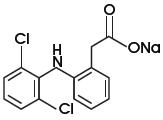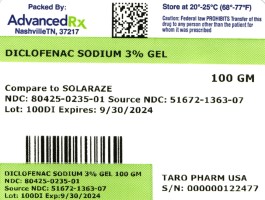 DRUG LABEL: Diclofenac Sodium
NDC: 80425-0235 | Form: GEL
Manufacturer: Advanced Rx Pharmacy of Tennessee, LLC
Category: prescription | Type: HUMAN PRESCRIPTION DRUG LABEL
Date: 20241231

ACTIVE INGREDIENTS: DICLOFENAC SODIUM 30 mg/1 g

Diclofenac Sodium Gel

SPL Unclassified

Rx Only

FOR DERMATOLOGIC USE ONLY. NOT FOR OPHTHALMIC USE.

Boxed Warning

WARNING: RISK OF SERIOUS CARDIOVASCULAR EVENTS

Cardiovascular Thrombotic Events

- Nonsteroidal anti-inflammatory drugs (NSAIDs) cause an increased risk of serious cardiovascular thrombotic events, including myocardial infarction and stroke, which can be fatal. This risk may occur early in treatment and may increase with duration of use.
- Diclofenac Sodium Gel is contraindicated in the setting of coronary artery bypass graft (CABG) surgery.

Description

Diclofenac Sodium Gel, 3%, contains the active ingredient, diclofenac sodium, in a clear, transparent, colorless to slightly yellow gel base. Diclofenac sodium is a white to slightly yellow crystalline powder. It is freely soluble in methanol, soluble in ethanol, sparingly soluble in water, slightly soluble in acetone, and partially insoluble in ether. The chemical name for diclofenac sodium is:

Sodium [o-(2,6-dichloranilino) phenyl] acetate

Diclofenac sodium has a molecular weight of 318.13.

The CAS number is CAS-15307-79-6. The structural formula is represented below:

Diclofenac Sodium Gel, 3% also contains benzyl alcohol, hyaluronate sodium, polyethylene glycol monomethyl ether, and purified water.

1 g of Diclofenac Sodium Gel contains 30 mg of the active substance, diclofenac sodium.

Clinical Pharmacology

The mechanism of action of diclofenac sodium in the treatment of actinic keratoses (AK) is unknown. The contribution to efficacy of individual components of the vehicle has not been established.

Pharmacokinetics

Absorption

When diclofenac sodium gel is applied topically, diclofenac is absorbed into the epidermis. In a study in patients with compromised skin (mainly atopic dermatitis and other dermatitic conditions) of the hands, arms or face, approximately 10% of the applied dose (2 grams of 3% gel over 100 cm2) of diclofenac was absorbed systemically in both normal and compromised epidermis after seven days, with four times daily applications.

After topical application of 2 g diclofenac sodium gel three times daily for six days to the calf of the leg in healthy subjects, diclofenac could be detected in plasma. Mean bioavailability parameters were AUC0-t 9±19 ng/hr/mL (mean±SD) with a Cmax of 4±5 ng/mL and a Tmax of 4.5±8 hours. In comparison, a single oral 75 mg dose of diclofenac (Voltaren®)1 produced an AUC of 1600 ng/hr/mL. Therefore, the systemic bioavailability after topical application of diclofenac sodium gel is lower than after oral dosing.

Comparative bioavailability studies have not been conducted between available diclofenac topical products (gels containing 1 to 3% diclofenac) which have different dosing regimens. A cross-study evaluation of the data indicates that diclofenac is more bioavailable when applied to diseased skin and less bioavailable when applied to intact skin.

Blood drawn at the end of treatment from 60 patients with AK lesions treated with diclofenac sodium gel in three adequate and well-controlled clinical trials was assayed for diclofenac levels. Each patient was administered 0.5 g of diclofenac sodium gel twice a day for up to 105 days. There were up to three 5 cm × 5 cm treatment sites per patient on the face, forehead, hands, forearm, and scalp. Serum concentrations of diclofenac were, on average, at or below 20 ng/mL. These data indicate that systemic absorption of diclofenac in patients treated topically with diclofenac sodium gel is much lower than that occurring after oral daily dosing of diclofenac sodium.

No information is available on the absorption of diclofenac when diclofenac sodium gel is used under occlusion.

1 Voltaren® is a registered trademark of its respective owner.

Distribution

Diclofenac binds tightly to serum albumin. The volume of distribution of diclofenac following oral administration is approximately 550 mL/kg.

Metabolism

Biotransformation of diclofenac following oral administration involves conjugation at the carboxyl group of the side chain or single or multiple hydroxylations resulting in several phenolic metabolites, most of which are converted to glucuronide conjugates. Two of these phenolic metabolites are biologically active, however to a much smaller extent than diclofenac. Metabolism of diclofenac following topical administration is thought to be similar to that after oral administration. The small amounts of diclofenac and its metabolites appearing in the plasma following topical administration makes the quantification of specific metabolites imprecise.

Elimination

Diclofenac and its metabolites are excreted mainly in the urine after oral dosing. Systemic clearance of diclofenac from plasma is 263±56 mL/min (mean±SD). The terminal plasma half-life is 1 to 2 hours. Four of the metabolites also have short terminal half-lives of 1 to 3 hours.

Indications and Usage

Diclofenac Sodium Gel is indicated for the topical treatment of actinic keratoses (AK). Sun avoidance is indicated during therapy.

Clinical Studies

Clinical trials were conducted involving a total of 427 patients (213 treated with diclofenac sodium gel and 214 with a gel vehicle). Each patient had no fewer than five AK lesions in a major body area, which was defined as one of five 5 cm × 5 cm regions: scalp, forehead, face, forearm and hand. Up to three major body areas were studied in any patient. All patients were 18 years of age or older (male and female) with no clinically significant medical problems outside of the AK lesions and had undergone a 60-day washout period from disallowed medications (masoprocol, 5-fluorouracil, cyclosporine, retinoids, trichloroacetic acid/lactic acid/peel, 50% glycolic acid peel) and hyaluronan-containing cosmetics. Patients were excluded from participation for reasons of known or suspected hypersensitivity to any diclofenac sodium gel ingredient, pregnancy, allergies to aspirin or other nonsteroidal anti-inflammatory drugs (NSAIDs), or other dermatological conditions which might affect the absorption of the study medication. Application of dermatologic products such as sunscreens, cosmetics, and other drug products was not permitted. Patients were instructed to apply a small amount of diclofenac sodium gel (approximately 0.5 g) onto the affected skin, using their fingers, and gently smoothing the gel over the lesion. In addition, all patients were instructed to avoid sun exposure. Complete clearing of the AK lesions 30 days after completion of treatment was the primary efficacy variable. No long-term patient follow-ups, after the 30-day assessments, were performed for the detection of recurrence.

Complete Clearance of Actinic Keratosis Lesions 30 Days Post-Treatment (all locations)

 | Diclofenac Sodium Gel | Vehicle | p-value
Study 1 90 days treatment | 27/58 (47%) | 11/59 (19%) | <0.001
Study 2 90 days treatment | 18/53 (34%) | 10/55 (18%) | 0.061
Study 3 60 days treatment | 15/48 (31%) | 5/49 (10%) | 0.021
30 days treatment | 7/49 (14%) | 2/49 (4%) | 0.221

Complete Clearance of Actinic Keratosis Lesions 30 Days Post-Treatment (by location)

 | Scalp | Forehead | Face | Arm/Forearm | Back of Hand
Study 1 90 days treatment
Diclofenac Sodium Gel | 1/4 (25%) | 17/30 (57%) | 9/17 (53%) | 4/12 (33%) | 6/16 (38%)
Vehicle | 3/9 (33%) | 8/24 (33%) | 5/17 (29%) | 4/12 (33%) | 0/14 (0)
p-value | 0.7646 | 0.0908 | 0.1682 | 1.000 | 0.0650
Study 2 90 days treatment
Diclofenac Sodium Gel | 2/6 (33%) | 9/19 (47%) | 4/5 (80%) | 5/8 (63%) | 1/17 (6%)
Vehicle | 0/4 (0) | 6/22 (27%) | 2/8 (25%) | 0/5 (0) | 3/16 (19%)
p-value | 0.4235 | 0.1870 | 0.0727 | 0.0888 | 0.2818
Study 3 60 days treatment
Diclofenac Sodium Gel | 3/7 (43%) | 13/31 (42%) | 10/19 (53%) | 0/1 (0) | 2/8 (25%)
Vehicle | 0/6 (0) | 5/36 (14%) | 2/13 (15%) | 0/2 (0) | 1/9 (11%)
p-value | 0.2271 | 0.0153 | 0.0433 | - | 0.4637
30 days treatment
Diclofenac Sodium Gel | 2/5 (40%) | 4/29 (14%) | 3/14 (21%) | 0/0 (0) | 0/9 (0)
Vehicle | 0/5 (0) | 2/29 (7%) | 2/18 (11%) | 0/1 (0) | 1/9 (11%)
p-value | 0.2299 | 0.3748 | 0.4322 | - | 0.6521
All data combined
Diclofenac Sodium Gel | 8/22 (36%) | 43/109 (39%) | 26/55 (47%) | 9/21 (43%) | 9/50 (18%)
Vehicle | 3/24 (13%) | 21/111 (19%) | 11/56 (20%) | 4/20 (20%) | 5/48 (10%)
p-value | 0.0903 | 0.0013 | 0.0016 | 0.2043 | 0.3662

Contraindications

Diclofenac Sodium Gel is contraindicated in patients with a known hypersensitivity to diclofenac, benzyl alcohol, polyethylene glycol monomethyl ether 350 and/or hyaluronate sodium.

Diclofenac Sodium Gel is contraindicated in the following patients:

- In the setting of coronary artery bypass graft (CABG) surgery.

Warnings and Precautions

Fetal Toxicity

Premature Closure of Fetal Ductus Arteriosus

Avoid use of NSAIDs, including diclofenac sodium gel, in pregnant women at about 30 weeks gestation and later. NSAIDs including diclofenac sodium gel, increase the risk of premature closure of the fetal ductus arteriosus at approximately this gestational age.

Oligohydramnios/Neonatal Renal Impairment

Use of NSAIDs, including diclofenac sodium gel, at about 20 weeks gestation or later in pregnancy may cause fetal renal dysfunction leading to oligohydramnios and, in some cases, neonatal renal impairment. These adverse outcomes are seen, on average, after days to weeks of treatment, although oligohydramnios has been infrequently reported as soon as 48 hours after NSAID initiation. Oligohydramnios is often, but not always, reversible with treatment discontinuation. Complications of prolonged oligohydramnios may, for example, include limb contractures and delayed lung maturation. In some postmarketing cases of impaired neonatal renal function, invasive procedures such as exchange transfusion or dialysis were required.

If NSAID treatment is necessary between about 20 weeks and 30 weeks gestation, limit diclofenac sodium gel use to the lowest effective dose and shortest duration possible. Consider ultrasound monitoring of amniotic fluid if diclofenac sodium gel treatment extends beyond 48 hours. Discontinue diclofenac sodium gel if oligohydramnios occurs and follow up according to clinical practice [see PRECAUTIONS; PREGNANCY].

As with other NSAIDs, anaphylactoid reactions may occur in patients without prior exposure to diclofenac. Diclofenac sodium should be given with caution to patients with the aspirin triad. The triad typically occurs in asthmatic patients who experience rhinitis with or without nasal polyps, or who exhibit severe, potentially fatal bronchospasm after taking aspirin or other NSAIDs.

Serious Skin Reactions, Drug Reaction with Eosinophilia and Systemic Symptoms (DRESS)

Drug Reaction with Eosinophilia and Systemic Symptoms (DRESS)

Drug Reaction with Eosinophilia and Systemic Symptoms (DRESS) has been reported in patients taking NSAIDs such as diclofenac sodium gel. Some of these events have been fatal or lifethreatening. DRESS typically, although not exclusively, presents with fever, rash, lymphadenopathy, and/or facial swelling. Other clinical manifestations may include hepatitis, nephritis, hematological abnormalities, myocarditis, or myositis. Sometimes symptoms of DRESS may resemble an acute viral infection. Eosinophilia is often present. Because this disorder is variable in its presentation, other organ systems not noted here may be involved. It is important to note that early manifestations of hypersensitivity, such as fever or lymphadenopathy, may be present even though rash is not evident. If such signs or symptoms are present, discontinue diclofenac sodium gel and evaluate the patient immediately.

Cardiovascular Thrombotic Events

Clinical trials of several COX-2 selective and nonselective NSAIDs of up to three years duration have shown an increased risk of serious cardiovascular (CV) thrombotic events, including myocardial infarction (MI) and stroke, which can be fatal. Based on available data, it is unclear that the risk for CV thrombotic events is similar for all NSAIDs. The relative increase in serious CV thrombotic events over baseline conferred by NSAID use appears to be similar in those with and without known CV disease or risk factors for CV disease. However, patients with known CV disease or risk factors had a higher absolute incidence of excess serious CV thrombotic events, due to their increased baseline rate. Some observational studies found that this increased risk of serious CV thrombotic events began as early as the first weeks of treatment. The increase in CV thrombotic risk has been observed most consistently at higher doses.

To minimize the potential risk for an adverse CV event in NSAID-treated patients, use the lowest effective dose for the shortest duration possible. Physicians and patients should remain alert for the development of such events, throughout the entire treatment course, even in the absence of previous CV symptoms. Patients should be informed about the symptoms of serious CV events and the steps to take if they occur.

There is no consistent evidence that concurrent use of aspirin mitigates the increased risk of serious CV thrombotic events associated with NSAID use. The concurrent use of aspirin and an NSAID, such as diclofenac, increases the risk of serious gastrointestinal (GI) events.

Status Post Coronary Artery Bypass Graft (CABG) Surgery

Two large, controlled clinical trials of a COX-2 selective NSAID for the treatment of pain in the first 10 to 14 days following CABG surgery found an increased incidence of myocardial infarction and stroke. NSAIDs are contraindicated in the setting of CABG.

Post-MI Patients

Observational studies conducted in the Danish National Registry have demonstrated that patients treated with NSAIDs in the post-MI period were at increased risk of reinfarction, CV-related death, and all-cause mortality beginning in the first week of treatment. In this same cohort, the incidence of death in the first year post MI was 20 per 100 person years in NSAID-treated patients compared to 12 per 100 person years in non-NSAID exposed patients. Although the absolute rate of death declined somewhat after the first year post-MI, the increased relative risk of death in NSAID users persisted over at least the next four years of follow-up.

Avoid the use of diclofenac sodium gel in patients with a recent MI unless the benefits are expected to outweigh the risk of recurrent CV thrombotic events. If diclofenac sodium gel is used in patients with a recent MI, monitor patients for signs of cardiac ischemia.

Heart Failure and Edema

The Coxib and traditional NSAID Trialists' Collaboration meta-analysis of randomized controlled trials demonstrated an approximately two-fold increase in hospitalizations for heart failure in COX-2 selective-treated patients and nonselective NSAID-treated patients compared to placebotreated patients. In a Danish National Registry study of patients with heart failure, NSAID use increased the risk of MI, hospitalization for heart failure, and death.

Additionally, fluid retention and edema have been observed in some patients treated with NSAIDs. Use of diclofenac may blunt the CV effects of several therapeutic agents used to treat these medical conditions [e.g., diuretics, ACE inhibitors, or angiotensin receptor blockers (ARBs)].

Avoid the use of diclofenac sodium gel in patients with severe heart failure unless the benefits are expected to outweigh the risk of worsening heart failure. If diclofenac sodium gel is used in patients with severe heart failure, monitor patients for signs of worsening heart failure.

General

Diclofenac sodium gel should be used with caution in patients with active gastrointestinal ulceration or bleeding and severe renal or hepatic impairments. Diclofenac sodium gel should not be applied to open skin wounds, infections, or exfoliative dermatitis. It should not be allowed to come in contact with the eyes.

The safety of the concomitant use of sunscreens, cosmetics or other topical medications and diclofenac sodium gel is unknown.

Information for Patients

Fetal Toxicity

If treatment with diclofenac sodium gel is needed for a pregnant woman between about 20 to 30 weeks gestation, advise her that she may need to be monitored for oligohydramnios, if treatment continues for longer than 48 hours. Inform pregnant women to avoid use of diclofenac sodium gel and other NSAIDs starting at 30 weeks gestation because of the risk of the premature closing of the fetal ductus arteriosus [see WARNINGS; FETAL TOXICITY, PRECAUTIONS; PREGNANCY].

In clinical studies, localized dermal side effects such as contact dermatitis, exfoliation, dry skin and rash were found in patients treated with diclofenac sodium gel at a higher incidence than in those with placebo.

Patients should understand the importance of monitoring and follow-up evaluation, the signs and symptoms of dermal adverse reactions, and the possibility of irritant or allergic contact dermatitis. If severe dermal reactions occur, treatment with diclofenac sodium gel may be interrupted until the condition subsides. Exposure to sunlight and the use of sunlamps should be avoided.

Safety and efficacy of the use of diclofenac sodium gel together with other dermal products, including cosmetics, sunscreens, and other topical medications on the area being treated, have not been studied.

Serious Skin Reactions, including DRESS

Advise patients to stop taking diclofenac sodium gel immediately if they develop any type of rash or fever and to contact their healthcare provider as soon as possible [see WARNINGS, SERIOUS SKIN REACTIONS].

Cardiovascular Thrombotic Events

Advise patients to be alert for the symptoms of cardiovascular thrombotic events, including chest pain, shortness of breath, weakness, or slurring of speech, and to report any of these symptoms to their health care provider immediately.

Heart Failure and Edema

Advise patients to be alert for the symptoms of congestive heart failure including shortness of breath, unexplained weight gain, or edema and to contact their healthcare provider if such symptoms occur.

Drug Interactions

Specific interaction studies between diclofenac sodium gel and other topical or oral agents were not performed.

Oral Nonsteroidal Anti-Inflammatory Drugs

Although low, there is systemic exposure to diclofenac following labeled use of diclofenac sodium gel. Therefore, concomitant administration of diclofenac sodium gel with oral NSAIDs or aspirin may result in increased NSAID adverse effects.

Carcinogenesis, Mutagenesis, Impairment of Fertility

There did not appear to be any increase in drug-related neoplasms following daily topical applications of diclofenac sodium gel for 2 years at concentrations up to 0.035% diclofenac sodium and 2.5% hyaluronate sodium in albino mice. (Note: diclofenac sodium gel contains 3% diclofenac sodium.)

When administered orally for 2 years, diclofenac showed no evidence of carcinogenic potential in rats given diclofenac sodium at up to 2 mg/kg/day (3 times the estimated systemic human exposure2), or in mice given diclofenac sodium at up to 0.3 mg/kg/day in males and 1 mg/kg/day in females (25% and 83%, respectively, of the estimated systemic human exposure).

A photococarcinogenicity study with up to 0.035% diclofenac in the diclofenac sodium gel vehicle gel was conducted in hairless mice at topical doses up to 2.8 mg/ kg/day. Median tumor onset was earlier in the 0.035% group (diclofenac sodium gel contains 3% diclofenac sodium).

Diclofenac was not genotoxic in in vitro point mutation assays in mammalian mouse lymphoma cells and Ames microbial test systems, or when tested in mammalian in vivo assays including dominant lethal and male germinal epithelial chromosomal studies in mice, and nucleus anomaly and chromosomal aberration studies in Chinese hamsters. It was also negative in the transformation assay utilizing BALB/3T3 mouse embryo cells.

Fertility studies have not been conducted with diclofenac sodium gel. Diclofenac sodium showed no evidence of impairment of fertility after oral treatment with 4 mg/kg/day (7 times the estimated systemic human exposure) in male or female rats.

2 Based on body surface area and assuming 10% bioavailability following topical application of 2 g diclofenac sodium gel per day (1 mg/kg diclofenac sodium).

Pregnancy

Risk Summary

Use of NSAIDs, including diclofenac sodium gel, can cause fetal renal dysfunction leading to oligohydramnios and, in some cases, neonatal renal impairment from 20 weeks of gestation, and premature closure of the fetal ductus arteriosus from 30 weeks of gestation. Because of these risks, limit dose and duration of diclofenac sodium gel use between about 20 and 30 weeks of gestation, and avoid diclofenac sodium gel use at about 30 weeks of gestation and later in pregnancy (see WARNINGS; FETAL TOXICITY).

Oligohydramnios/Neonatal Renal Impairment

Use of NSAIDs at about 20 weeks gestation or later in pregnancy has been associated with cases of fetal renal dysfunction leading to oligohydramnios, and in some cases, neonatal renal impairment.

Premature Closure of Fetal Ductus Arteriosus

Use of NSAIDs, including diclofenac sodium gel, at about 30 weeks gestation or later in pregnancy increases the risk of premature closure of the fetal ductus arteriosus.

Data from observational studies regarding other potential embryofetal risks of NSAID use in women in the first or second trimesters of pregnancy are inconclusive. In the general U.S. population, all clinically recognized pregnancies, regardless of drug exposure, have a background rate of 2 to 4% for major malformations, and 15 to 20% for pregnancy loss.

In animal reproduction studies, no evidence of teratogenicity was observed in mice, rats, or rabbits given diclofenac during the period of organogenesis at doses at least 15 times, the maximum recommended human dose (MRHD) of diclofenac sodium gel (see ANIMAL DATA).

Based on published animal data, prostaglandins have been shown to have an important role in endometrial vascular permeability, blastocyst implantation, and decidualization, and administration of prostaglandin synthesis inhibitors such as diclofenac sodium, resulted in increased pre-and post-implantation loss. Prostaglandins also have been shown to have an important role in fetal kidney development. In published animal studies, prostaglandin synthesis inhibitors have been reported to impair kidney development when administered at clinically relevant doses.

The safety of diclofenac sodium gel has not been established during pregnancy.

Clinical Considerations

Fetal/Neonatal Adverse Reactions

Premature Closure of Fetal Ductus Arteriosus

Avoid use of NSAIDs in women at about 30 weeks gestation and later in pregnancy, because NSAIDs, including diclofenac sodium gel, can cause premature closure of the fetal ductus arteriosus (see WARNINGS; FETAL TOXICITY).

Oligohydramnios/Neonatal Renal Impairment

If an NSAID is necessary at about 20 weeks gestation or later in pregnancy, limit the use to the lowest effective dose and shortest duration possible. If diclofenac sodium gel treatment extends beyond 48 hours, consider monitoring with ultrasound for oligohydramnios. If oligohydramnios occurs, discontinue diclofenac sodium gel and follow up according to clinical practice (see WARNINGS; FETAL TOXICITY).

Data

Human Data

Premature Closure of Fetal Ductus Arteriosus

Published literature reports that the use of NSAIDs at about 30 weeks of gestation and later in pregnancy may cause premature closure of the fetal ductus arteriosus.

Oligohydramnios/Neonatal Renal Impairment

Published studies and postmarketing reports describe maternal NSAID use at about 20 weeks gestation or later in pregnancy associated with fetal renal dysfunction leading to oligohydramnios, and in some cases, neonatal renal impairment. These adverse outcomes are seen, on average, after days to weeks of treatment, although oligohydramnios has been infrequently reported as soon as 48 hours after NSAID initiation. In many cases, but not all, the decrease in amniotic fluid was transient and reversible with cessation of the drug. There have been a limited number of case reports of maternal NSAID use and neonatal renal dysfunction without oligohydramnios, some of which were irreversible. Some cases of neonatal renal dysfunction required treatment with invasive procedures, such as exchange transfusion or dialysis.

Methodological limitations of these postmarketing studies and reports include lack of a control group; limited information regarding dose, duration, and timing of drug exposure; and concomitant use of other medications. These limitations preclude establishing a reliable estimate of the risk of adverse fetal and neonatal outcomes with maternal NSAID use. Because the published safety data on neonatal outcomes involved mostly preterm infants, the generalizability of certain reported risks to the full-term infant exposed to NSAIDs through maternal use is uncertain.

Animal Data

Reproductive studies performed with diclofenac sodium alone at oral doses up to 20 mg/kg/day (15 times the estimated systemic human exposure3) in mice, 10 mg/kg/day (15 times the estimated systemic human exposure) in rats, and 10 mg/kg/day (30 times the estimated systemic human exposure) in rabbits have revealed no evidence of teratogenicity despite the induction of maternal toxicity. In rats, maternally toxic doses were associated with dystocia, prolonged gestation, reduced fetal weights and growth, and reduced fetal survival. Diclofenac has been shown to cross the placental barrier in mice and rats.

3 Based on body surface area and assuming 10% bioavailability following topical application of 2 g diclofenac sodium gel per day (1 mg/kg diclofenac sodium)

Labor and Delivery

The effects of diclofenac on labor and delivery in pregnant women are unknown. Because of the known effects of prostaglandin-inhibiting drugs on the fetal cardiovascular system (closure of the ductus arteriosus), use of diclofenac during late pregnancy should be avoided and, as with other nonsteroidal anti-inflammatory drugs, it is possible that diclofenac may inhibit uterine contractions and delay parturition.

Nursing Mothers

Because of the potential for serious adverse reactions in nursing infants from diclofenac sodium, a decision should be made whether to discontinue nursing or to discontinue the drug, taking into account the importance of the drug to the mother.

Pediatric Use

Actinic keratoses is not a condition seen within the pediatric population. Diclofenac sodium gel should not be used by children.

Geriatric Use

Of the 211 subjects treated with diclofenac sodium gel in controlled clinical studies, 143 subjects were 65 and over. Of those 143 subjects, 55 subjects were 75 and over. No overall differences in safety or effectiveness were observed between these subjects and younger subjects, and other reported clinical experience has not identified differences in responses between the elderly and younger patients, but greater sensitivity of some older individuals cannot be ruled out.

Adverse Reactions

Of the 423 patients evaluable for safety in adequate and well-controlled trials, 211 were treated with diclofenac sodium gel drug product and 212 were treated with a vehicle gel. Eighty-seven percent (87%) of the diclofenac sodium gel-treated patients (183 patients) and 84% of the vehicletreated patients (178 patients) experienced one or more adverse events (AEs) during the studies. The majority of these reactions were mild to moderate in severity and resolved upon discontinuation of therapy.

Of the 211 patients treated with diclofenac sodium gel, 172 (82%) experienced AEs involving skin and the application site compared to 160 (75%) vehicle-treated patients. Application site reactions (ASRs) were the most frequent AEs in both diclofenac sodium gel- and vehicle-treated groups. Of note, four reactions, contact dermatitis, rash, dry skin and exfoliation (scaling) were significantly more prevalent in the diclofenac sodium gel group than in the vehicle-treated patients.

Eighteen percent of diclofenac sodium gel-treated patients and 4% of vehicle-treated patients discontinued from the clinical trials due to adverse events (whether considered related to treatment or not). These discontinuations were mainly due to skin irritation or related cutaneous adverse reactions.

Table 1 below presents the AEs reported at an incidence of >1% for patients treated with either diclofenac sodium gel or vehicle (60- and 90-day treatment groups) during the phase 3 studies.

Table 1. Adverse Events Reported (>1% in Any Treatment Group) During Diclofenac Sodium Gel Phase 3 Clinical Trials Incidences for 60-Day and 90-Day Treatments

 | 60-day Treatment |  | 90-day Treatment
 | Diclofenac Sodium Gel (%) N=48 | Gel Vehicle (%) N=49 | Diclofenac Sodium Gel (%) N=114 | Gel Vehicle (%) N=114
BODY AS A WHOLE | 21 | 20 | 20 | 18
Abdominal Pain | 2 | 0 | 1 | 0
Accidental Injury | 0 | 0 | 4 | 2
Allergic Reaction | 0 | 0 | 1 | 3
Asthenia | 0 | 0 | 2 | 0
Back Pain | 4 | 0 | 2 | 2
Chest Pain | 2 | 0 | 1 | 0
Chills | 0 | 2 | 0 | 0
Flu Syndrome | 10 | 6 | 1 | 4
Headache | 0 | 6 | 7 | 6
Infection | 4 | 6 | 4 | 5
Neck Pain | 0 | 0 | 2 | 0
Pain | 2 | 0 | 2 | 2
CARDIOVASCULAR SYSTEM | 2 | 4 | 3 | 1
Hypertension | 2 | 0 | 1 | 0
Migraine | 0 | 2 | 1 | 0
Phlebitis | 0 | 2 | 0 | 0
DIGESTIVE SYSTEM | 4 | 0 | 6 | 8
Constipation | 0 | 0 | 0 | 2
Diarrhea | 2 | 0 | 2 | 3
Dyspepsia | 2 | 0 | 3 | 4
METABOLIC AND NUTRITIONAL DISORDERS | 2 | 8 | 7 | 2
Creatine Phosphokinase Increased | 0 | 0 | 4 | 1
Creatinine Increased | 2 | 2 | 0 | 1
Edema | 0 | 2 | 0 | 0
Hypercholesteremia | 0 | 2 | 1 | 0
Hyperglycemia | 0 | 2 | 1 | 0
SGOT Increased | 0 | 0 | 3 | 0
SGPT Increased | 0 | 0 | 2 | 0
MUSCULOSKELETAL SYSTEM | 4 | 0 | 3 | 4
Arthralgia | 2 | 0 | 0 | 2
Arthrosis | 2 | 0 | 0 | 0
Myalgia | 2 | 0 | 3 | 1
NERVOUS SYSTEM | 2 | 2 | 2 | 5
Anxiety | 0 | 2 | 0 | 1
Dizziness | 0 | 0 | 0 | 4
Hypokinesia | 2 | 0 | 0 | 0
RESPIRATORY SYSTEM | 8 | 8 | 7 | 6
Asthma | 2 | 0 | 0 | 0
Dyspnea | 2 | 0 | 2 | 0
Pharyngitis | 2 | 8 | 2 | 4
Pneumonia | 2 | 0 | 0 | 1
Rhinitis | 2 | 2 | 2 | 2
Sinusitis | 0 | 0 | 2 | 0
SKIN AND APPENDAGES | 75 | 86 | 86 | 71
Acne | 0 | 2 | 0 | 1
Application Site Reaction | 75 | 71 | 84 | 70
Acne | 0 | 4 | 1 | 0
Alopecia | 2 | 0 | 1 | 1
Contact Dermatitis | 19 | 4 | 33 | 4
Dry Skin | 27 | 12 | 25 | 17
Edema | 4 | 0 | 3 | 0
Exfoliation | 6 | 4 | 24 | 13
Hyperesthesia | 0 | 0 | 3 | 1
Pain | 15 | 22 | 26 | 30
Paresthesia | 8 | 4 | 20 | 20
Photosensitivity Reaction | 0 | 2 | 3 | 0
Pruritus | 31 | 59 | 52 | 45
Rash | 35 | 20 | 46 | 17
Vesiculobullous Rash | 0 | 0 | 4 | 1
Contact Dermatitis | 2 | 0 | 0 | 0
Dry Skin | 0 | 4 | 3 | 0
Herpes Simplex | 0 | 2 | 0 | 0
Maculopapular Rash | 0 | 2 | 0 | 0
Pain | 2 | 2 | 1 | 0
Pruritus | 4 | 6 | 4 | 1
Rash | 2 | 10 | 4 | 0
Skin Carcinoma | 0 | 6 | 2 | 2
Skin Nodule | 0 | 2 | 0 | 0
Skin Ulcer | 2 | 0 | 1 | 0
SPECIAL SENSES | 2 | 0 | 4 | 2
Conjunctivitis | 2 | 0 | 4 | 1
Eye Pain | 0 | 2 | 2 | 0
UROGENITAL SYSTEM | 0 | 0 | 4 | 5
Hematuria | 0 | 0 | 2 | 1
OTHER | 0 | 0 | 0 | 3
Procedure | 0 | 0 | 0 | 3

Skin and Appendages Adverse Events Reported for Diclofenac Sodium Gel at Less Than 1% Incidence in the Phase 3 Studies: skin hypertrophy, paresthesia, seborrhea, urticaria, application site reactions (skin carcinoma, hypertonia, skin hypertrophy lacrimation disorder, maculopapular rash, purpuric rash, vasodilation).

Adverse Reactions Reported for Oral Diclofenac Dosage Form (not topical diclofenac sodium gel)

Body as a Whole: abdominal pain or cramps4, headache4, fluid retention4, abdominal distention4, malaise, swelling of lips and tongue, photosensitivity, anaphylaxis, anaphylactoid reactions, chest pain.

Cardiovascular: hypertension, congestive heart failure, palpitations, flushing, tachycardia, premature ventricular contractions, myocardial infarction, hypotension.

Digestive: diarrhea4, indigestion4, nausea4, constipation4, flatulence4, liver test abnormalities4, PUB4, i.e., peptic ulcer, with or without bleeding and/or perforation, or bleeding without ulcer, vomiting, jaundice, melena, esophageal lesions, aphthous stomatitis, dry mouth and mucous membranes, bloody diarrhea, hepatitis, hepatic necrosis, cirrhosis, hepatorenal syndrome, appetite change, pancreatitis with or without concomitant hepatitis, colitis, intestinal perforation.

Hemic and Lymphatic: hemoglobin decrease, leukopenia, thrombocytopenia, eosinophilia, hemolytic anemia, aplastic anemia, agranulocytosis, purpura, allergic purpura, bruising.

Metabolic and Nutritional Disorders: azotemia, hypoglycemia, weight loss.

Nervous System: dizziness4, insomnia, drowsiness, depression, diplopia, anxiety, irritability, aseptic meningitis, convulsions, paresthesia, memory disturbance, nightmares, tremor, tic, abnormal coordination, disorientation, psychotic reaction.

Respiratory: epistaxis, asthma, laryngeal edema, dyspnea, hyperventilation, edema of pharynx.

Skin and Appendages: rash4, pruritus4, alopecia, urticaria, eczema, dermatitis, bullous eruption, erythema multiforme major, angioedema, Stevens-Johnson syndrome, excess perspiration, exfoliative dermatitis.

Special Senses: tinnitus4, blurred vision, taste disorder, reversible and irreversible hearing loss, scotoma, vitreous floaters, night blindness, amblyopia.

Urogenital: nephrotic syndrome, proteinuria, oliguria, interstitial nephritis, papillary necrosis, acute renal failure, urinary frequency, nocturia, hematuria, impotence, vaginal bleeding.

4 Incidence Greater than 1% marked with asterisk

Overdosage

Due to the low systemic absorption of topically-applied diclofenac sodium gel, overdosage is unlikely. There have been no reports of ingestion of diclofenac sodium gel. In the event of oral ingestion, resulting in significant systemic side effects, it is recommended that the stomach be emptied by vomiting or lavage. Forced diuresis may theoretically be beneficial because the drug is excreted in the urine. The effect of dialysis or hemoperfusion in the elimination of diclofenac (99% protein-bound) remains unproven. In addition to supportive measures, the use of oral activated charcoal may help to reduce the absorption of diclofenac. Supportive and symptomatic treatment should be given for complications such as renal failure, convulsions, gastrointestinal irritation and respiratory depression.

Dosage and Administration

Diclofenac sodium gel is applied to lesion areas twice daily. It is to be smoothed onto the affected skin gently. The amount needed depends upon the size of the lesion site. Assure that enough diclofenac sodium gel is applied to adequately cover each lesion. Normally 0.5 g of gel is used on each 5 cm × 5 cm lesion site. The recommended duration of therapy is from 60 days to 90 days. Complete healing of the lesion(s) or optimal therapeutic effect may not be evident for up to 30 days following cessation of therapy. Lesions that do not respond to therapy should be carefully reevaluated and management reconsidered.

How Supplied/Storage and Handling

Diclofenac Sodium Gel, 3% is available in 100 g (NDC 80425-0235-01) tubes. Each gram of gel contains 30 mg of diclofenac sodium.

Store at 20° to 25°C (68° to 77°F) [see USP Controlled Room Temperature]. Protect from heat. Avoid freezing.

SPL Unclassified Section

Manufactured by: Taro Pharmaceuticals Inc., Brampton, Ontario, Canada L6T 1C1
Distributed by: Taro Pharmaceuticals U.S.A., Inc., Hawthorne, NY 10532
TARO is a registered trademark of Taro Pharmaceuticals U.S.A., Inc.

Distributed by: Advanced Rx Pharmacy of Tennessee, LLC
Revised: September 2021

Medguide

Medication Guide
Diclofenac (dye-KLOE-fen-ak)
Sodium Gel, 3%

What is the most important information I should know about Diclofenac Sodium Gel and medicines called Nonsteroidal Anti-inflammatory Drugs (NSAIDs)?

Diclofenac Sodium Gel is an NSAID medicine that is used on the skin only (topical). Do not use Diclofenac Sodium Gel in or on the eyes.

NSAIDs can cause serious side effects, including:

- Increased risk of a heart attack or stroke that can lead to death. This risk may happen early in treatment and may increase:
  - with increasing doses of NSAIDs
  - with longer use of NSAIDs

Do not take or use NSAIDs right before or after a heart surgery called a "coronary artery bypass graft (CABG)". Avoid taking NSAIDs after a recent heart attack, unless your healthcare provider tells you to. You may have an increased risk of another heart attack if you take or use NSAIDs after a recent heart attack.

- Increased risk of bleeding, ulcers, and tears (perforation) of the esophagus (tube leading from the mouth to the stomach), stomach and intestines:< >anytime during usewithout warning symptomsthat may cause deathpast history of stomach ulcers, or stomach or intestinal bleeding with use of NSAIDs
- taking medicines called "corticosteroids", "anticoagulants", "SSRIs", or "SNRIs"
- increasing doses of NSAIDs
- longer use of NSAIDs
- smoking
- drinking alcohol
- older age
- poor health
- advanced liver disease
- bleeding problems

NSAIDs should only be used:

- exactly as prescribed
- at the lowest dose possible for your treatment
- for the shortest time needed

What is Diclofenac Sodium Gel?

Diclofenac Sodium Gel is an NSAID that is used on the skin (topical) to treat a skin condition called actinic keratosis.

Diclofenac Sodium Gel is not for use in children.

Who should not use Diclofenac Sodium Gel?

Do not use Diclofenac Sodium Gel:

- if you have had an allergic reaction to any of the ingredients in Diclofenac Sodium Gel. See the end of this Medication Guide for a complete list of ingredients in Diclofenac Sodium Gel.
- right before or after heart bypass surgery.

Before using Diclofenac Sodium Gel, tell your healthcare provider about all of your medical conditions, including if you:

- have liver or kidney problems
- have high blood pressure
- have asthma
- are pregnant or plan to become pregnant. Taking NSAIDs at about 20 weeks of pregnancy or later may harm your unborn baby. If you need to take NSAIDs for more than 2 days when you are between 20 and 30 weeks of pregnancy, your healthcare provider may need to monitor the amount of fluid in your womb around your baby. You should not take NSAIDs after about 30 weeks of pregnancy.
- are breastfeeding or plan to breastfeed. You and your healthcare provider should decide if you will use Diclofenac Sodium Gel or breastfeed. You should not do both.

Tell your healthcare provider about all of the medicines you take, including prescription or over-the-counter medicines, vitamins, or herbal supplements. NSAIDs and some other medicines can interact with each other and cause serious side effects. Do not start taking any new medicine without talking to your healthcare provider first.

How should I use Diclofenac Sodium Gel?

- Use Diclofenac Sodium Gel exactly as your healthcare provider tells you to use it.
- Apply Diclofenac Sodium Gel 2 times a day.
- Apply enough Diclofenac Sodium Gel to cover each skin lesion and gently rub in.
- Diclofenac Sodium Gel may be used for 60 to 90 days. You may not see improvement of skin lesions for up to 30 days after stopping treatment. See your healthcare provider if lesions do not respond to treatment.
- Wash your hands after applying Diclofenac Sodium Gel.

What should I avoid while using Diclofenac Sodium Gel?

- Avoid spending time in sunlight or artificial light, such as tanning beds or sunlamps. Diclofenac Sodium Gel can make your skin sensitive to sunlight and the light from tanning beds and sunlamps.
- You should avoid applying Diclofenac Sodium Gel to open skin wounds, skin infections, or peeling skin.

What are the possible side effects of Diclofenac Sodium Gel?

Diclofenac Sodium Gel and other NSAIDs can cause serious side effects, including:

See "WHAT IS THE MOST IMPORTANT INFORMATION I SHOULD KNOW ABOUT DICLOFENAC SODIUM GEL AND MEDICINES CALLED NONSTEROIDAL ANTI-INFLAMMATORY DRUGS (NSAIDS)?"

- new or worse high blood pressure
- heart failure
- liver problems including liver failure
- kidney problems including kidney failure
- low red blood cells (anemia)
- life-threatening skin reactions
- life threatening allergic reactions

Other side effects of NSAIDs include: stomach pain, constipation, diarrhea, gas, heartburn, nausea, vomiting, and dizziness.

Get emergency help right away if you get any of the following symptoms:

- shortness of breath or trouble breathing
- chest pain
- weakness in one part or side of your body
- slurred speech
- swelling of the face or throat

Stop using Diclofenac Sodium Gel and call your healthcare provider right away if you get any of the following symptoms:

- nausea
- more tired or weaker than usual
- diarrhea
- itching
- your skin or eyes look yellow
- indigestion or stomach pain
- flu-like symptoms
- vomit blood
- there is blood in your bowel movement or it is black and sticky like tar
- unusual weight gain
- skin rash or blisters with fever
- swelling of the arms, legs, hands and feet

Application site skin reactions are common with Diclofenac Sodium Gel and include: skin redness, itching, rash, dry skin, scaling, and peeling.

If Diclofenac Sodium Gel is accidentally taken by mouth, call your healthcare provider or get medical help right away.

These are not all the possible side effects of NSAIDs. For more information, ask your healthcare provider or pharmacist about NSAIDs.

Call your doctor for medical advice about side effects. You may report side effects to FDA at 1-800-FDA-1088.

Other information about NSAIDs

Aspirin is an NSAID but it does not increase the chance of a heart attack. Aspirin can cause bleeding in the brain, stomach, and intestines. Aspirin can also cause ulcers in the stomach and intestines.

Some NSAIDs are sold in lower doses without a prescription (over-the-counter). Talk to your healthcare provider before using over-the-counter NSAIDs for more than 10 days.

How should I store Diclofenac Sodium Gel?

- Store Diclofenac Sodium Gel at room temperature 68°F to 77°F (20°C to 25°C).
- Keep Diclofenac Sodium Gel away from heat. Avoid freezing Diclofenac Sodium Gel.

Keep Diclofenac Sodium Gel and all medicines out of the reach of children.

General information about the safe and effective use of Diclofenac Sodium Gel

Medicines are sometimes prescribed for purposes other than those listed in a Medication Guide. Do not use Diclofenac Sodium Gel for a condition for which it was not prescribed. Do not give Diclofenac Sodium Gel to other people, even if they have the same symptoms that you have. It may harm them.

If you would like more information about Diclofenac Sodium Gel, talk with your healthcare provider. You can ask your pharmacist or healthcare provider for information about Diclofenac Sodium Gel that is written for health professionals.

What are the ingredients in Diclofenac Sodium Gel?

Active ingredient: diclofenac sodium

Inactive ingredient: benzyl alcohol, hyaluronate sodium, polyethylene glycol monomethyl ether, and purified water.

Manufactured by: Taro Pharmaceuticals Inc., Brampton, Ontario, Canada L6T 1C1

Distributed by: Taro Pharmaceuticals U.S.A., Inc., Hawthorne, NY 10532

For more information, call 1-866-923-4914.

This Medication Guide has been approved by the U.S. Food and Drug Administration.
Revised: September 2021